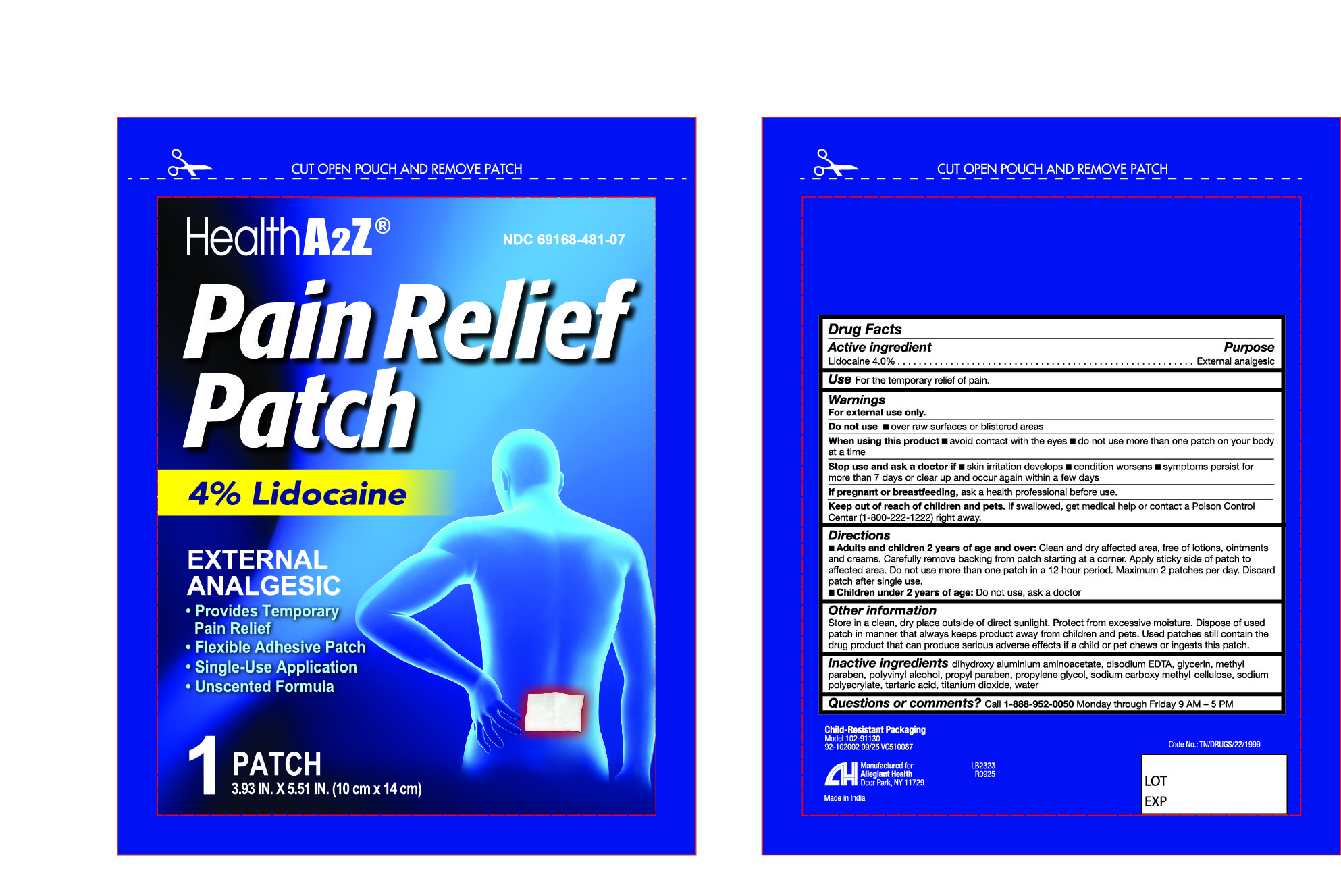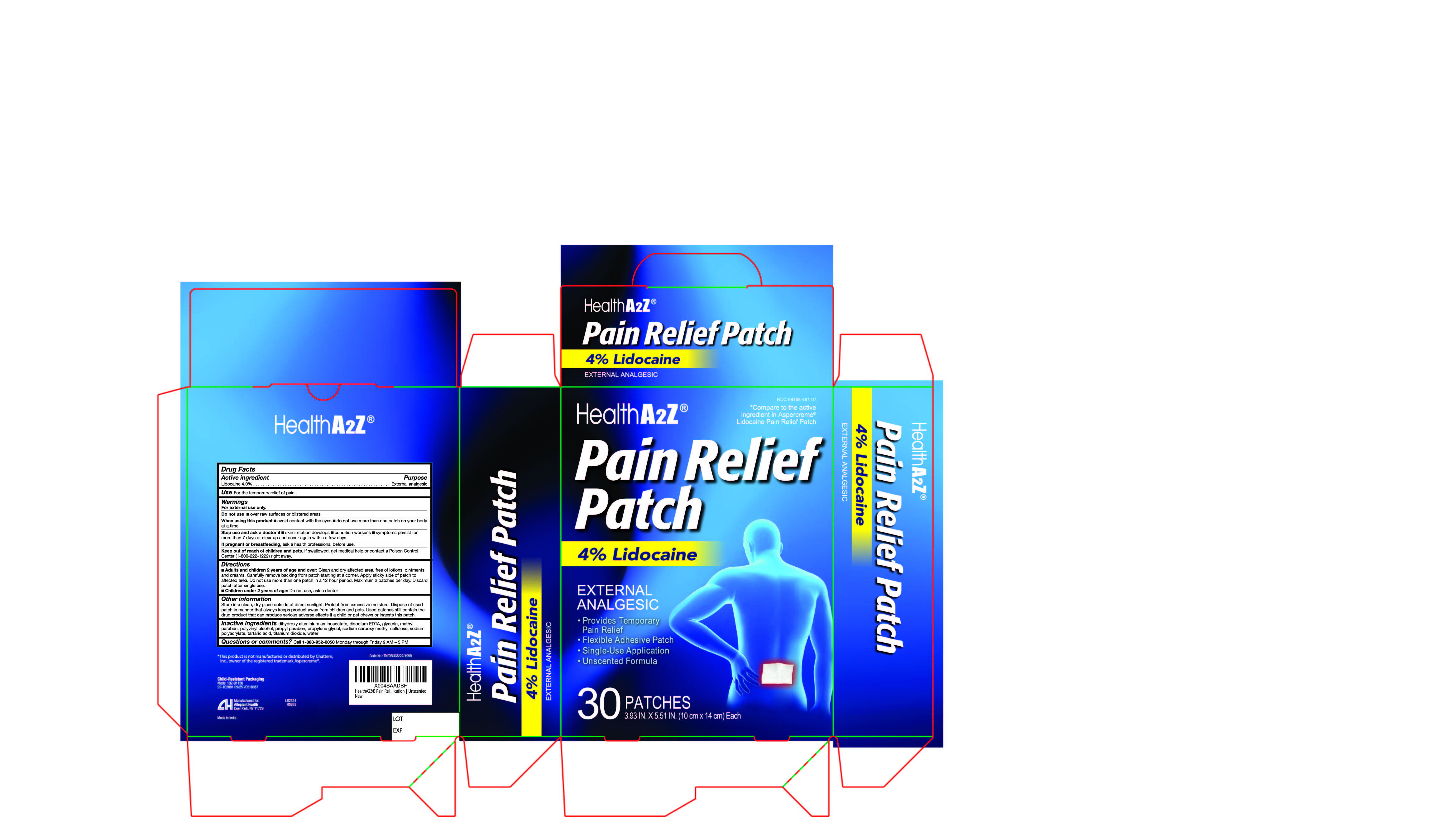 DRUG LABEL: Lidocaine Pain Relief
NDC: 69168-481 | Form: PATCH
Manufacturer: Allegiant Health
Category: otc | Type: HUMAN OTC DRUG LABEL
Date: 20251230

ACTIVE INGREDIENTS: LIDOCAINE 0.04 g/100 g
INACTIVE INGREDIENTS: SODIUM POLYACRYLATE (2500000 MW); POLYVINYL ALCOHOL; DIHYDROXYALUMINUM AMINOACETATE; GLYCERIN; METHYLPARABEN; PROPYLENE GLYCOL; PROPYLPARABEN; TARTARIC ACID; WATER; CARBOXYMETHYLCELLULOSE SODIUM, UNSPECIFIED FORM; TITANIUM DIOXIDE

481 - Lidocaine Pain Relief Patch

Active ingredient(s)

Lidocaine 4%

Purpose

Topical anesthetic

Use(s)

For temporary relief of pain

Warnings

For external use only

Do not use if you have

- more than one patch on your body at a time
- on cut or swollen skin
- on puncture wounds
- For more than one week without consulting a doctor if you are allergic to any active or inactive ingredients
- if pouch is damaged or opened

When using this product

- use only as directed
- read and follow all directions and warnings on this carton
- Do not allow contact with the eyes
- Do not use at the same time as other topical analgesics
- do not bandage tightly or apply local heat (such as heating pads) to the area of use
- Do not microwave
- Dispose of a used patch in a manner that always keeps the product away from children and pets. Used patches still contain the drug product that can produce serious adverse effects if a child or pet chews or ingest this patch.

Stop use and ask a doctor if

- conditions worsen
- Redness is present
- Irritation develops
- symptoms persist for more than 7 days or clear up and occur again within a few days
- you experience signs of an injury, such as pain, swelling, or blistering where the product was applied.

If pregnant or breastfeeding,

ask a health professional before use.

Keep out of reach of children and pets

If swallowed, get medical help or contact a Poison Control Center 800-222-1222 right away.

Directions

Adults and children 12 years of age and over:

- clean and dry affected area
- carefully remove the backing from the patch starting at a corner
- Apply the sticky side of patch to the affected area.
- Use one patch for up to 12 hours
- Discard patch after single use

Children under 12 years of age: consult a physician.

Other information

- store in a clean, dry place outside of direct sunlight. Protect from excessive moisture.

Inactive ingredients

dihydroxy aluminium aminoacetate, disodium EDTA, glycerin, methyl paraben, polyacrylic acid, polyvinyl alcohol, propyl paraben, propylene glycol, sodium carboxy methyl cellulose, sodium polyacrylate, tartaric acid, titanium dioxide, water

Questions/Comments

Call 1-888-952-0050

(Monday-Friday 9 AM – 5 PM EST)